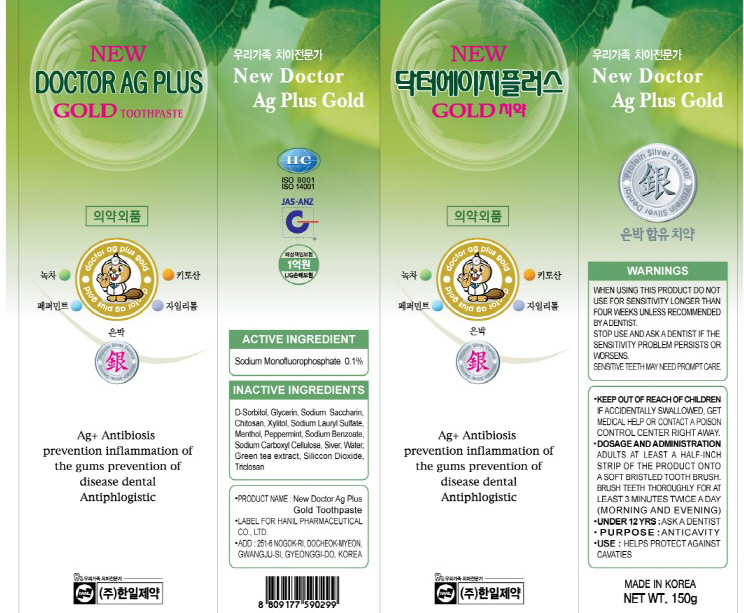 DRUG LABEL: NEW DOCTOR AG PLUS
NDC: 75984-001 | Form: PASTE, DENTIFRICE
Manufacturer: HANIL PHARMACEUTICAL CO., LTD.
Category: otc | Type: HUMAN OTC DRUG LABEL
Date: 20110225

ACTIVE INGREDIENTS: SODIUM MONOFLUOROPHOSPHATE 0.15 g/150 g
INACTIVE INGREDIENTS: GLYCERIN; XYLITOL; SODIUM LAURYL SULFATE; MENTHOL; PEPPERMINT; SODIUM BENZOATE; SILVER; WATER

Drug Facts

ACTIVE INGREDIENT: Sodium Monofluorophosphate

INACTIVE INGREDIENTS:

D-Sorbitol, Glycerin, Sodium Saccharin, Chitosan, Xylitol, Sodium Lauryl Sulfate, Menthol, Peppermint, Sodium Benzoate, Green tea extract, Sodium Carboxyl Cellulose,
Siver, Water, Triclosan, Siliccon Dioxide

PURPOSE: ANTICAVITY

WARNINGS:
WHEN USING THIS PRODUCT DO NOT USE FOR SENSITIVITY LONGER THAN FOUR WEEKS UNLESS RECOMMENDED BY A DENTIST.
STOP USE AND ASK A DENTIST IF THE SENSITIVITY PROBLEM PERSISTS OR WORSENS.
SENSITIVE TEETH MAY NEED PROMPT CARE.

KEEP OUT OF REACH OF CHILDREN:

IF ACCIDENTALLY SWALLOWED, GET MEDICAL HELP OR CONTACT A POISON CONTROL CENTER RIGHT AWAY.

INDICATION AND USAGE:

ADULTS AT LEAST A HALF-INCH STRIP OF THE PRODUCT ONTO A SOFT BRISTLED TOOTH BRUSH.
BRUSH TEETH THOROUGHLY FOR AT LEAST 3 MINUTES TWICE A DAY (MORNING AND EVENING)
UNDER 12 YRS: ASK A DENTIST

DOSAGE AND ADMINISTRATION:

ADULTS AT LEAST A HALF-INCH STRIP OF THE PRODUCT ONTO A SOFT BRISTLED TOOTH BRUSH.
BRUSH TEETH THOROUGHLY FOR AT LEAST 3 MINUTES TWICE A DAY (MORNING AND EVENING)
UNDER 12 YRS: ASK A DENTIST